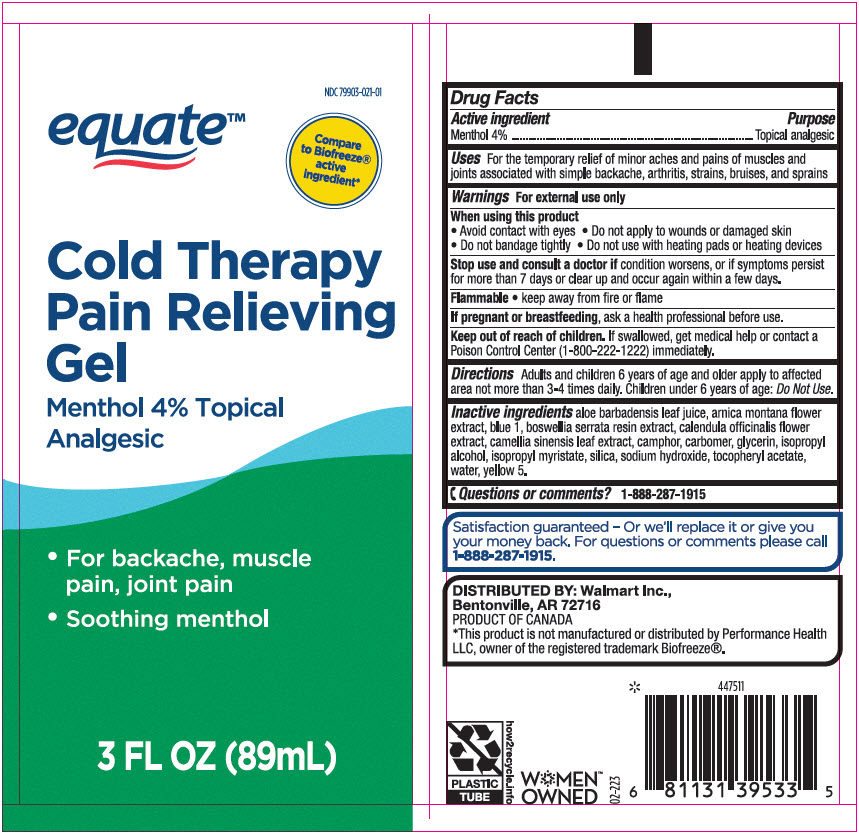 DRUG LABEL: Equate Cold Therapy Pain Relieving
NDC: 79903-021 | Form: GEL
Manufacturer: Wal-Mart Stores, Inc.
Category: otc | Type: HUMAN OTC DRUG LABEL
Date: 20241118

ACTIVE INGREDIENTS: MENTHOL, UNSPECIFIED FORM 40 mg/1 mL
INACTIVE INGREDIENTS: ALOE VERA LEAF; ARNICA MONTANA FLOWER; FD&C BLUE NO. 1; INDIAN FRANKINCENSE; CALENDULA OFFICINALIS FLOWER; GREEN TEA LEAF; CAMPHOR (SYNTHETIC); CARBOMER HOMOPOLYMER, UNSPECIFIED TYPE; Glycerin; Isopropyl Alcohol; Isopropyl Myristate; SILICON DIOXIDE; Sodium Hydroxide; .ALPHA.-TOCOPHEROL ACETATE, DL-; Water; FD&C YELLOW NO. 5

Equate™ Cold Therapy Pain Relieving Gel
Topical Analgesic

Drug Facts

Active ingredient

Menthol 4%

Purpose

Topical analgesic

Uses

for the temporary relief of minor aches and pains of muscles and joints associated with simple backache, arthritis, strains, bruises, and sprains

Warnings

For external use only

When using this product

- avoid contact with eyes
- do not apply to wounds or damaged skin
- do not bandage tightly
- do not use with heating pads or other heating devices

Stop use and consult a doctor if condition worsens, or if symptoms persist for more than 7 days or clear up and occur again within a few days.

Flammable

- keep away from fire or flame

PREGNANCY OR BREAST FEEDING

If pregnant or breast-feeding, ask a health professional before use.

Keep out of reach of children. If swallowed, get medical help or contact a Poison Control Center (1-800-222-1222) immediately.

Directions

adults and children 6 years of age and older apply to affected area not more than 3-4 times daily. Children under 6 years of age: Do Not Use.

Inactive ingredients

aloe barbadensis leaf juice, arnica montana flower extract, blue 1, boswellia serrata resin extract, calendula officinalis flower extract, camellia sinensis leaf extract, camphor, carbomer, glycerin, isopropyl alcohol, isopropyl myristate, silica, sodium hydroxide, tocopheryl acetate, water, yellow 5.

Questions or comments?

1-888-287-1915

DISTRIBUTED BY: Walmart Inc.,
Bentonville, AR 72716

PRINCIPAL DISPLAY PANEL - 89 mL Tube Label

NDC 79903-021-01

equate™

Compare
to Biofreeze®
active
ingredient*

Cold Therapy
Pain Relieving
Gel

Menthol 4% Topical
Analgesic

- For backache, muscle
  pain, joint pain
- Soothing menthol

3 FL OZ (89mL)